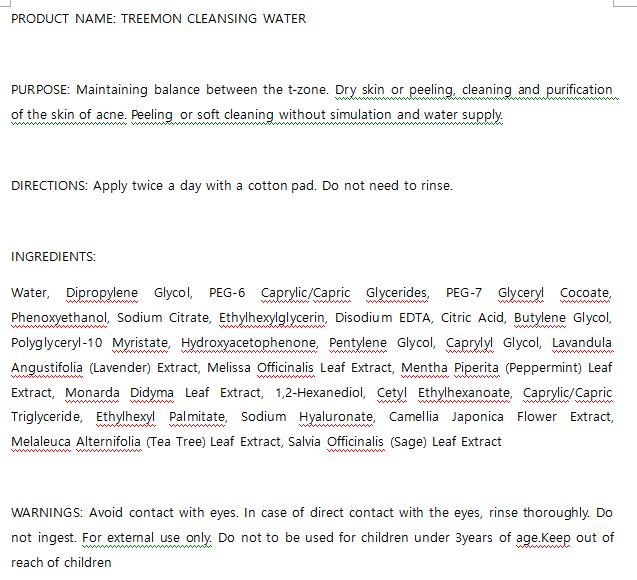 DRUG LABEL: W.SKIN TREEMON CLEANSING WATER
NDC: 74997-0022 | Form: LIQUID
Manufacturer: J&J COMPANY
Category: otc | Type: HUMAN OTC DRUG LABEL
Date: 20210508

ACTIVE INGREDIENTS: CITRIC ACID MONOHYDRATE 0.03 g/100 mL
INACTIVE INGREDIENTS: HYALURONATE SODIUM; WATER

J&J COMPANY - STOP-AGING PEPTIDE TONER

ACTIVE INGREDIENT

citric acid

INACTIVE INGREDIENT

Water, Dipropylene Glycol, PEG-6 Caprylic/Capric Glycerides, PEG-7 Glyceryl Cocoate, Phenoxyethanol, Sodium Citrate, Ethylhexylglycerin, Disodium EDTA, Citric Acid, Butylene Glycol, Polyglyceryl-10 Myristate, Hydroxyacetophenone, Pentylene Glycol, Caprylyl Glycol, Lavandula Angustifolia (Lavender) Extract, Melissa Officinalis Leaf Extract, Mentha Piperita (Peppermint) Leaf Extract, Monarda Didyma Leaf Extract, 1,2-Hexanediol, Cetyl Ethylhexanoate, Caprylic/Capric Triglyceride, Ethylhexyl Palmitate, Sodium Hyaluronate, Camellia Japonica Flower Extract, Melaleuca Alternifolia (Tea Tree) Leaf Extract, Salvia Officinalis (Sage) Leaf Extract

PURPOSE

Maintaining balance between the t-zone. Dry skin or peeling, cleaning and purification of the skin of acne. Peeling or soft cleaning without simulation and water supply

keep out of reach of the children

INDICATIONS AND USAGE

Apply twice a day with a cotton pad. Do not need to rinse.

WARNINGS

Avoid contact with eyes. In case of direct contact with the eyes, rinse thoroughly. Do not ingest. For external use only. Do not to be used for children under 3years of age.Keep out of reach of children

DOSAGE AND ADMINISTRATION

for external use only